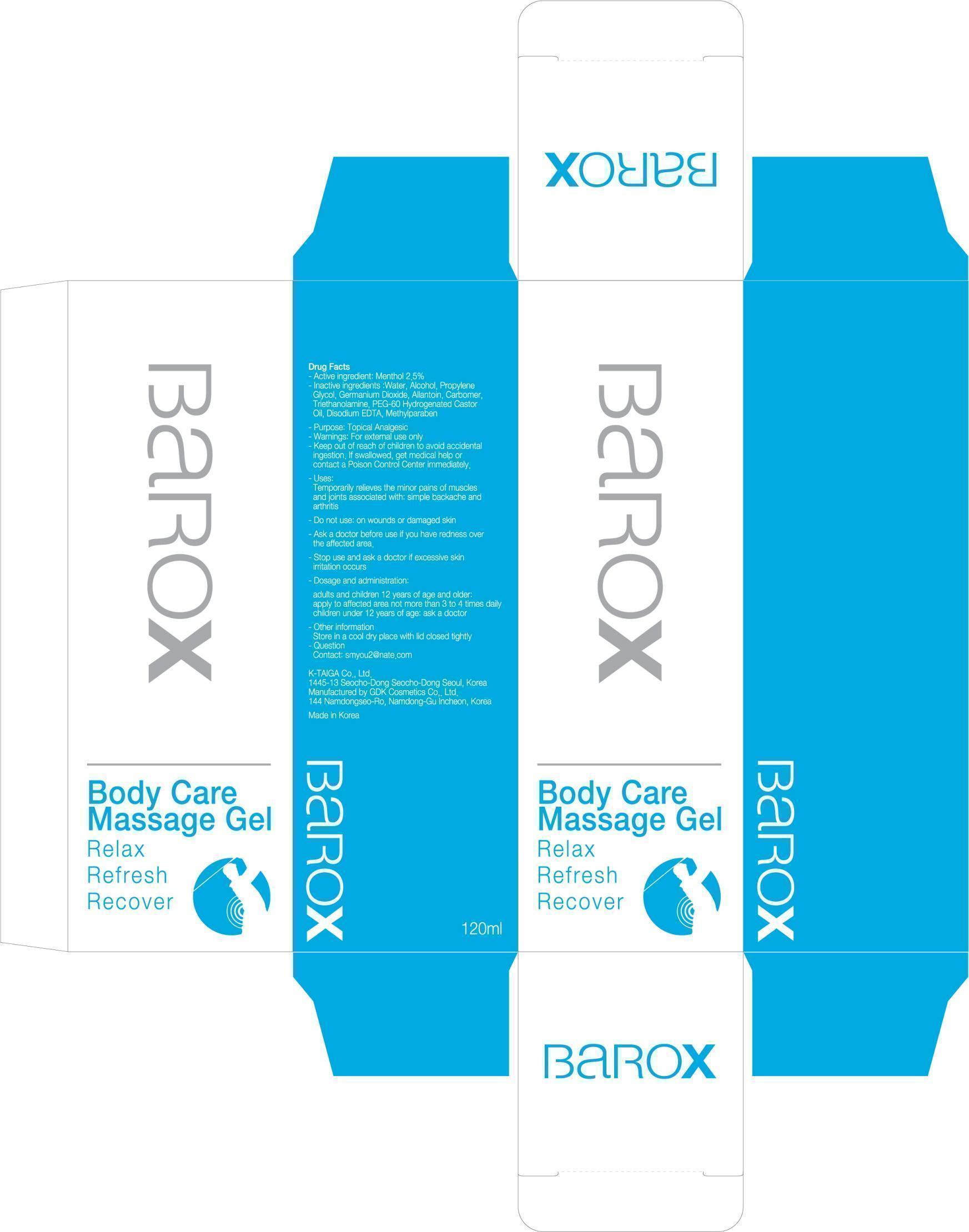 DRUG LABEL: BAROX
NDC: 52227-100 | Form: GEL
Manufacturer: KTAIGA CO., LTD.
Category: otc | Type: HUMAN OTC DRUG LABEL
Date: 20120815

ACTIVE INGREDIENTS: MENTHOL 3 g/120 mL
INACTIVE INGREDIENTS: WATER 82.2 g/120 mL; ALCOHOL 18 g/120 mL; PROPYLENE GLYCOL 4.8 g/120 mL; GERMANIUM DIOXIDE 0.96 g/120 mL; TROLAMINE 0.6 g/120 mL

Active ingredient

Active ingredient: Menthol 2.5%

Inactive ingredient

Inactive ingredients:
Water, Alcohol, Propylene Glycol, Germanium Dioxide, Allantoin, Carbomer, Triethanolamine, PEG-60 Hydrogenated Castor Oil, Disodium EDTA, Methylparaben

Purpose

Purpose: Topical Analgesic

Warnings

Warnings: For external use only

Keep out of reach of children

Keep out of reach of children to avoid accidental ingestion.
If swallowed, get medical help or contact a Poison Control Center immediately.

Uses

Temporarily relieves the minor pains of muscles and joints associated with:
simple backache and arthritis

Dosage and administration

adults and children 12 years of age and older: apply to affected area not more than 3 to 4 times daily
children under 12 years of age: ask a doctor

Description

Ask a doctor before use if you have redness over the affected area.

Do not use: on wounds or damaged skin

Stop use and ask a doctor if excessive skin irritation occurs.

Other information:
Store in a cool dry place with lid closed tightly

Question
Contact: smyou2@nate.com